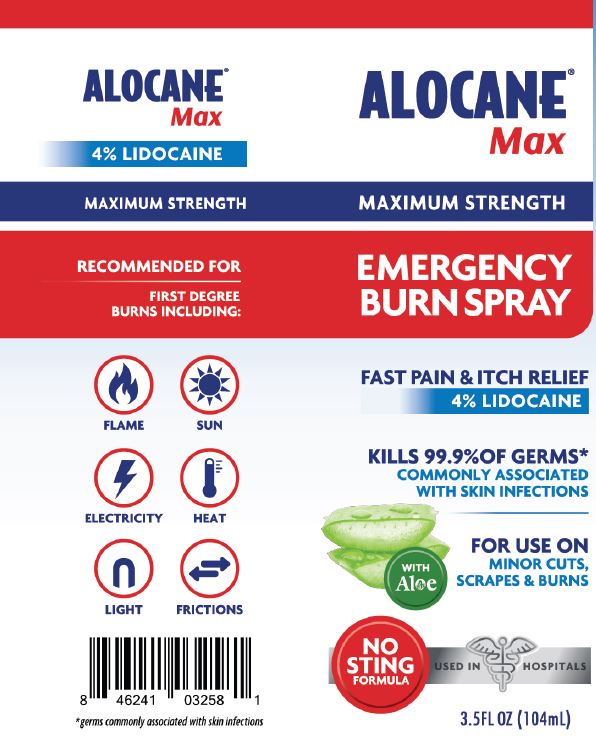 DRUG LABEL: Alocane Max
NDC: 68229-408 | Form: SPRAY
Manufacturer: Quest Products LLC
Category: otc | Type: HUMAN OTC DRUG LABEL
Date: 20251204

ACTIVE INGREDIENTS: LIDOCAINE HYDROCHLORIDE 4 g/100 mL; BENZALKONIUM CHLORIDE 0.13 g/100 mL
INACTIVE INGREDIENTS: PROPANEDIOL; ALOE VERA LEAF; DIMETHYL ISOSORBIDE; HYDROXYETHYL CELLULOSE (5500 MPA.S AT 2%); PHENOXYETHANOL; CAPRYLYL GLYCOL; CHLORPHENESIN; .ALPHA.-TOCOPHEROL ACETATE; WATER

Alocane® Max Spray

Drug Facts

ACTIVE INGREDIENT

Active Ingredient | Purpose
Benzalkonium Chloride 0.13%; Lidocaine HCL 4% | First Aid Antiseptic; Topical Analgesic

Uses:

First aid to help prevent bacterial icontamination or skin infection, and for temporary relief of pain and itching associated with minor:

- Burns
- Cuts
- Sunburn
- Scrapes
- Minor Skin Irritation

Warnings

For external use only.

Ask a doctor before use if you have:

- Deep or puncture wounds
- Animal Bites
- Serious burns

Do not use:

- In or near the eyes
- In large quantities or over large areas of the body
- On raw surfaces or blistered areas

Stop use and ask doctor: if condition worsens, or if symptoms persist for more than 7 days or clear up and occur again within a few days.

PREGNANCY OR BREAST FEEDING

If pregnant or breast-feeding, ask a health care professional before use.

Keep out of reach of children. If swallowed, get medical help or call a Poison Control Center right away.

Directions

Adults and children 2 years of age and older: Clean the affected area. Spray a small amount on the affected area 3 to 4 times daily. May be covered with a sterile bandage (let dry first). To apply to the face, spray on palm and apply.

Children under 2 years of age: ask a doctor.

Other Information

Store at 15°-30°C (59°-86°F)

Inactive Ingredients

Aloe Barbadensis (Aloe) Leaf Juice, Caprylyl Glycol, Chlorphenesin, Dimethyl Isosorbide, Hydroxyethyl Cellulose, Phenoxyethanol, Propanediol, Tocopheryl Acetate (Vitamin E), Water.